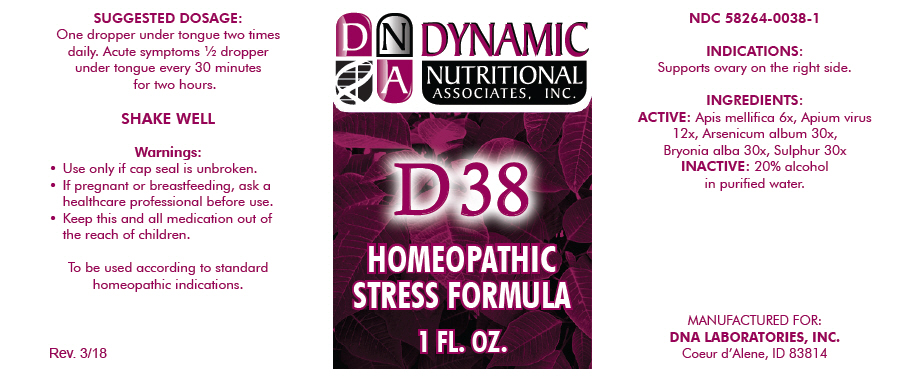 DRUG LABEL: D-38
NDC: 58264-0038 | Form: SOLUTION
Manufacturer: DNA Labs, Inc.
Category: homeopathic | Type: HUMAN OTC DRUG LABEL
Date: 20250113

ACTIVE INGREDIENTS: APIS MELLIFERA 6 [hp_X]/1 mL; APIS MELLIFERA VENOM 12 [hp_X]/1 mL; ARSENIC TRIOXIDE 30 [hp_X]/1 mL; BRYONIA ALBA ROOT 30 [hp_X]/1 mL; SULFUR 30 [hp_X]/1 mL
INACTIVE INGREDIENTS: ALCOHOL; WATER

D-38

NDC 58264-0038-1

INDICATIONS

PURPOSE

Supports ovary on the right side.

INGREDIENTS

ACTIVE

Apis mellifica 6x, Apium virus 12x, Arsenicum album 30x, Bryonia alba 30x, Sulphur 30x

INACTIVE

20% alcohol in purified water.

SUGGESTED DOSAGE

One dropper under tongue two times daily. Acute symptoms ½ dropper under tongue every 30 minutes for two hours.

STORAGE AND HANDLING

SHAKE WELL

Warnings

- Use only if cap seal is unbroken.

PREGNANCY OR BREAST FEEDING

- If pregnant or breastfeeding, ask a healthcare professional before use.

KEEP OUT OF REACH OF CHILDREN

- Keep this and all medication out of the reach of children.

To be used according to standard homeopathic indications.

PRINCIPAL DISPLAY PANEL - 1 FL. OZ. Bottle Label

DYNAMIC
NUTRITIONAL
ASSOCIATES, INC.

D 38

HOMEOPATHIC
STRESS FORMULA

1 FL. OZ.